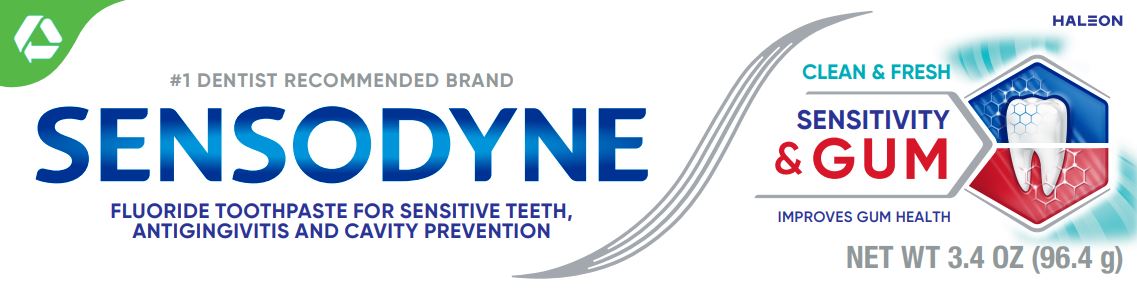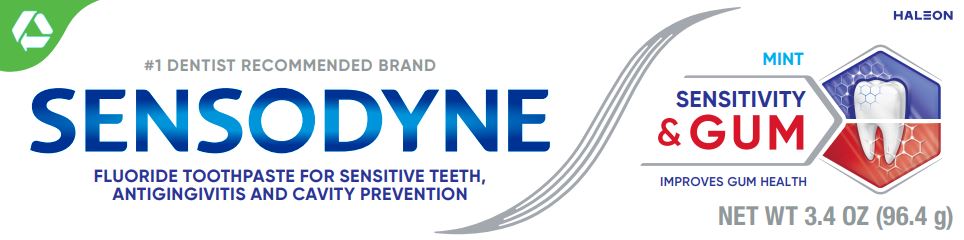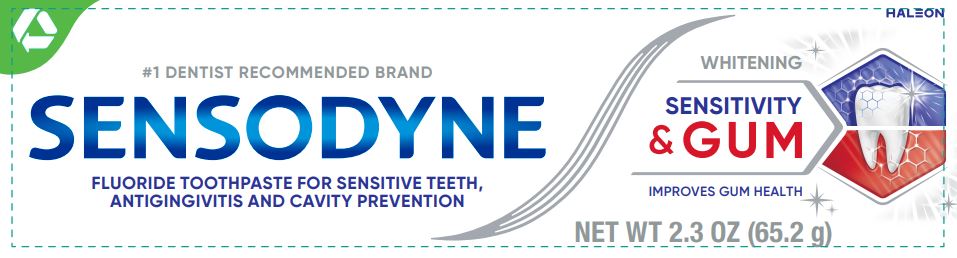 DRUG LABEL: SENSODYNE

NDC: 0135-5023 | Form: PASTE
Manufacturer: Haleon US Holdings LLC
Category: otc | Type: HUMAN OTC DRUG LABEL
Date: 20240307

ACTIVE INGREDIENTS: STANNOUS FLUORIDE 1.1 mg/1 g
INACTIVE INGREDIENTS: GLYCERIN; POLYETHYLENE GLYCOL 400; HYDRATED SILICA; SODIUM TRIPOLYPHOSPHATE, UNSPECIFIED FORM; SODIUM LAURYL SULFATE; TITANIUM DIOXIDE; COCAMIDOPROPYL BETAINE; SACCHARIN SODIUM

Drug Facts

Active ingredient

Stannous fluoride 0.454% (0.15% w/v fluoride ion)

Purposes

Anticavity, Antigingivitis, Antihypersensitivity

Uses

- aids in the prevention of dental cavities.
- helps control bleeding gums.
- helps interfere with harmful effects of plaque associated with gingivitis.
- builds increasing protection against painful sensitivity of the teeth to cold, heat, acids, sweets or contact.

Warnings

Stop use and ask a dentist if

- the problem persists or worsens. Sensitive teeth may indicate a serious problem that may need prompt care by a dentist.
- pain/sensitivity still persists after 4 weeks of use.
- gingivitis, bleeding, or redness persists for more than 2 weeks.
- you have painful or swollen gums, pus from the gum line, loose teeth, or increasing spacing between the teeth. These maybe signs or symptoms of periodontitis, a serious form of gum disease.

Keep out of reach of children.

If more than used for brushing is accidentally swallowed, get medical help or contact a Poison Control Center right away.

Directions

- adults and children 12 years of age and older:
  - apply at least a 1-inch strip of the product onto a soft bristle toothbrush.
  - brush teeth thoroughly for at least 1 minute twice a day (morning and evening), and not more than 3 times a day, or as recommended by a dentist or doctor. Make sure to brush all sensitive areas of the teeth. Minimize swallowing. Spit out after brushing.
- children under 12 years of age:Consult a dentist or doctor.

Other information

- products containing stannous fluoride may produce surface staining of the teeth. Adequate toothbrushing may prevent these stains which are not harmful or permanent and may be removed by your dentist.
- this product is specifically formulated to help prevent staining.
- do not store above 30°C (86°F)

Inactive ingredients (Sensitivity & Gum Whitening)

glycerin, PEG-8, hydrated silica, pentasodium triphosphate, flavor, sodium lauryl sulfate, titanium dioxide, polyacrylic acid, cocamidopropyl betaine, sodium saccharin

Inactive ingredients (Sensitivity & Gum Mint)

glycerin, PEG-8, hydrated silica, pentasodium triphosphate, flavor, sodium lauryl sulfate, titanium dioxide, polyacrylic acid, cocamidopropyl betaine, sodium saccharin

Inactive ingredients (Clean & Fresh)

glycerin, PEG-8, hydrated silica, pentasodium triphosphate, flavor, sodium lauryl sulfate, titanium dioxide, polyacrylic acid, cocamidopropyl betaine, sodium saccharin

Questions or comments?

1-866-844-2797

Additional Information (Whitening)

ALWAYS FOLLOW THE LABEL

Dual Action for TOOTH SENSITIVITY & GUM PROBLEMS

SENSITIVE AREAS AND SWOLLEN, BLEEDING GUMS

BUILDS A PROTECTIVE LAYER OVER SENSITIVE AREAS

TARGETS AND HELPS REMOVE PLAQUE BACTERIA

RELIEVES TOOTH SENSITIVITY* AND IMPROVES GUM HEALTH

Why use Sensodyne Sensitivity & Gum?

Sensodyne Sensitivity & Gum contains a clinically proven ingredient to relieve tooth sensitivity and improve gum health. It builds a protective layer over sensitive areas, effectively relieving tooth sensitivity. It targets and removes plaque bacteria associated with gingivitis, to help reduce swollen, bleeding gums. You can deal with both these concerning problems with one specialist toothpaste. Sensodyne Sensitivity & Gum is a daily fluoride toothpaste.

*with twice daily brushing

Trademarks are owned by or licensed to the Haleon group of companies.

©2023 Haleon group of companies or its licensor.

Distributed by: Haleon, Warren, NJ 07059

Pat. Info www.productpats.com

†Recycling facilities for this product may not exist in your area

CARTONRECYCLE

TUBERECYCLE

CAPCHECK LOCALLY†

Additional Information (Mint and Clean & Fresh)

SENSODYNE

SENSITIVITY & GUM

Tooth sensitivity & gum problems?

Many people with sensitive teeth also have gum problems. Tooth sensitivity can occur when exposed dentin comes into contact with cold, hot, sweet and sour. Early gum problems are caused by a build-up of plaque bacteria, which can lead to redness, swelling, and bleeding.

SENSITIVE AREAS AND SWOLLEN, BLEEDING GUMS

BUILDS A PROTECTIVE LAYER OVER SENSITIVE AREAS

TARGETS AND HELPS REMOVE PLAQUE BACTERIA

RELIEVES TOOTH SENSITIVITY* AND IMPROVES GUM HEALTH

Dual Action for TOOTH SENSITIVITY & GUM PROBLEMS

*with twice daily brushing

Why use Sensodyne Sensitivity & Gum?

Sensodyne Sensitivity & Gum contains a clinically proven ingredient to relieve tooth sensitivity and improve gum health. It builds a protective layer over sensitive areas, effectively relieving tooth sensitivity. It targets and removes plaque bacteria associated with gingivitis, to help reduce swollen, bleeding gums. You can deal with both these concerning problems with one specialist toothpaste. Sensodyne Sensitivity & Gum is a daily fluoride toothpaste.

Trademarks are owned by or licensed to the Haleon group of companies.

©2023 Haleon group of companies or its licensor.

Distributed by: Haleon, Warren, NJ 07059

Pat. Info www.productpats.com

†Recycling facilities for this product may not exist in your area

CARTONRECYCLE

TUBERECYCLE

CAPCHECK LOCALLY†

Principal Display Panel (Whitening)

#1 DENTIST RECOMMENDED BRAND

SENSODYNE

FLUORIDE TOOTHPASTE FOR SENSITIVE TEETH, ANTIGINGIVITIS AND CAVITY PROTECTION

WHITENING

SENSITIVITY & GUM

IMPROVES GUM HEALTH

NET WT 2.3 OZ (65.2 g)

62000000207518

Principal Display Panel (Mint)

#1 DENTIST RECOMMENDED BRAND

SENSODYNE

FLUORIDE TOOTHPASTE FOR SENSITIVE TEETH, ANTIGINGIVITIS AND CAVITY PROTECTION

MINT

SENSITIVITY & GUM

IMPROVES GUM HEALTH

NET WT 3.4 OZ (96.4 g)

62000000207515

Principal Display Panel (Clean & Fresh)

#1 DENTIST RECOMMENDED BRAND

SENSODYNE

FLUORIDE TOOTHPASTE FOR SENSITIVE TEETH, ANTIGINGIVITIS AND CAVITY PROTECTION

CLEAN & FRESH

SENSITIVITY & GUM

IMPROVES GUM HEALTH

NET WT 3.4 OZ (96.4 g)

62000000207513